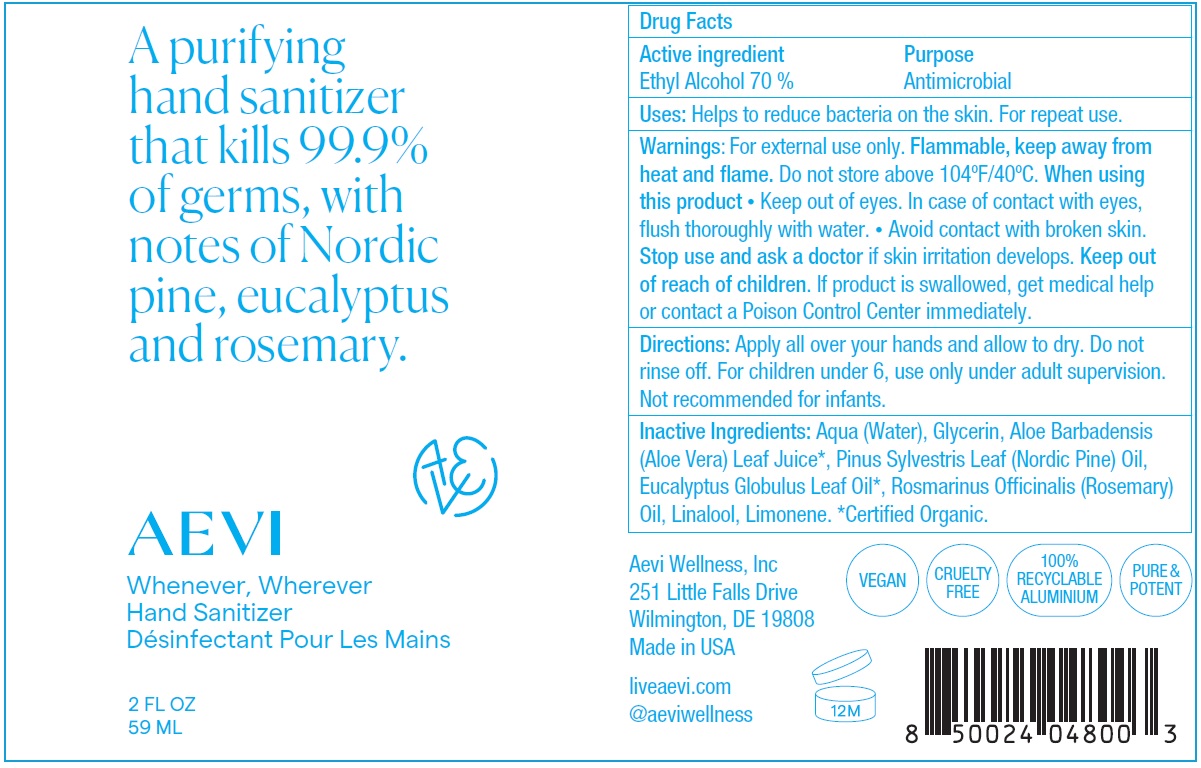 DRUG LABEL: Aevi Whenever Wherever Hand Sanitizer
NDC: 62742-4203 | Form: SPRAY
Manufacturer: Allure Labs Inc
Category: otc | Type: HUMAN OTC DRUG LABEL
Date: 20210301

ACTIVE INGREDIENTS: ALCOHOL 70 mL/100 mL
INACTIVE INGREDIENTS: GLYCERIN; EUCALYPTUS OIL; PINE NEEDLE OIL (PINUS SYLVESTRIS); ROSMARINUS OFFICINALIS FLOWERING TOP OIL; LIMONENE, (+)-; WATER; ALOE VERA LEAF; LINALOOL, (+/-)-

Drug Facts

Active Ingredient

Ethyl Alcohol 70%

Purpose

Antimicrobial

Uses:

Helps to reduce bacteria on the skin. For repeat use.

Warnings

For external use only. Flammable, keep away from heat and flame. Do not store above 104ºF/40ºC.

When using this product

• Keep out of eyes. In case of contact with eyes, flush thoroughly with water.

• Avoid contact with broken skin.

Stop use and ask a doctor if skin irritation develops.

Keep out of reach of children. If product is swallowed, get medical help or contact a Poison Control Center immediately.

Directions:

Apply all over your hands and allow to dry. Do not rinse off. For children under 6, use only under adult supervision. Not recommended for infants.

Inactive Ingredients

Aqua (Water), Glycerin, Aloe Barbadensis (Aloe Vera) Leaf Juice*, Pinus Sylvestris Leaf (Nordic Pine) Oil, Eucalyptus Globulus Leaf Oil*, Rosmarinus Officinalis (Rosemary) Oil, Linalool, Limonene.

PACKAGE LABEL

Aevi Wellness, Inc
251 Little Falls Drive
Wilmington, DE 19808
Made in USA